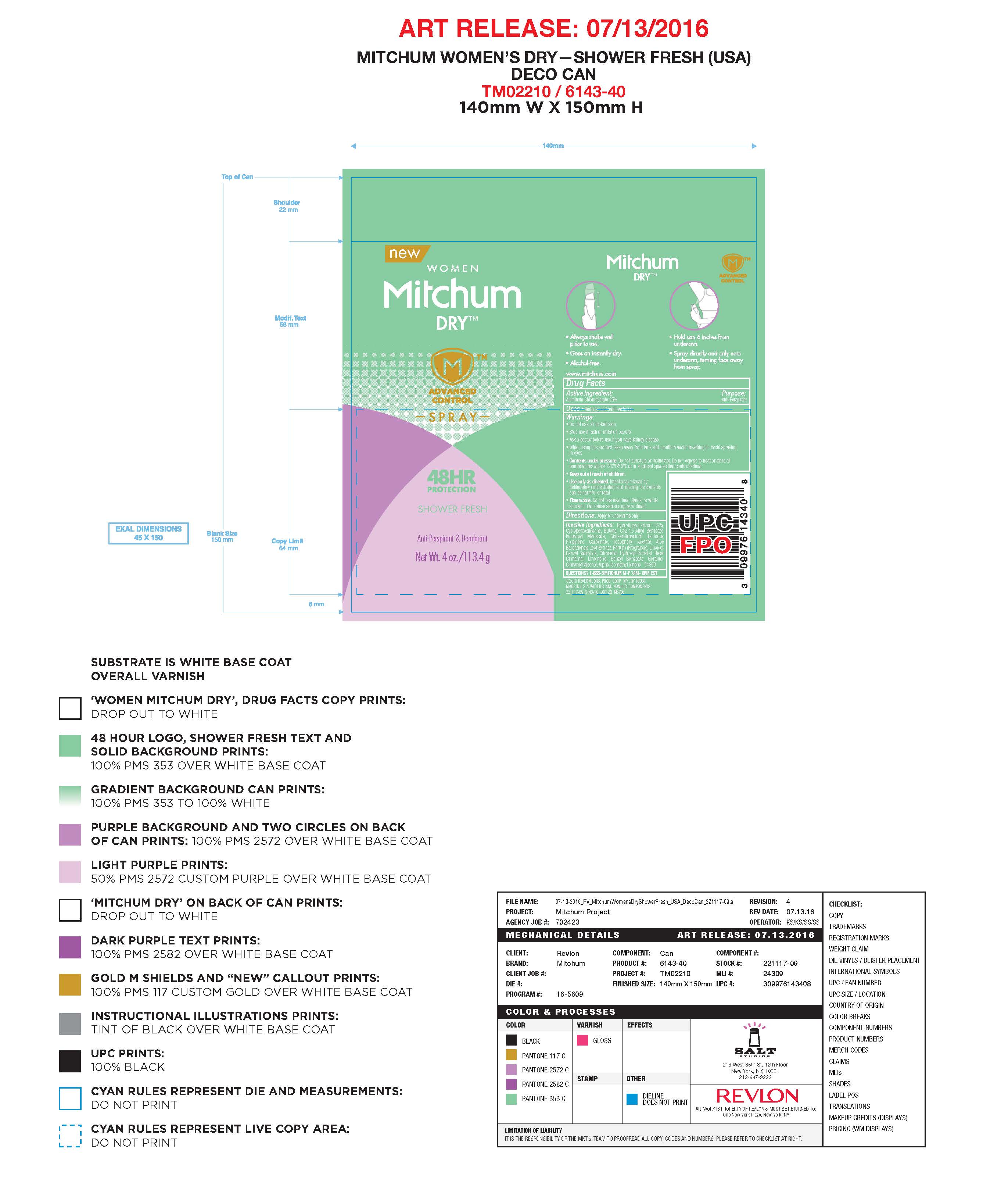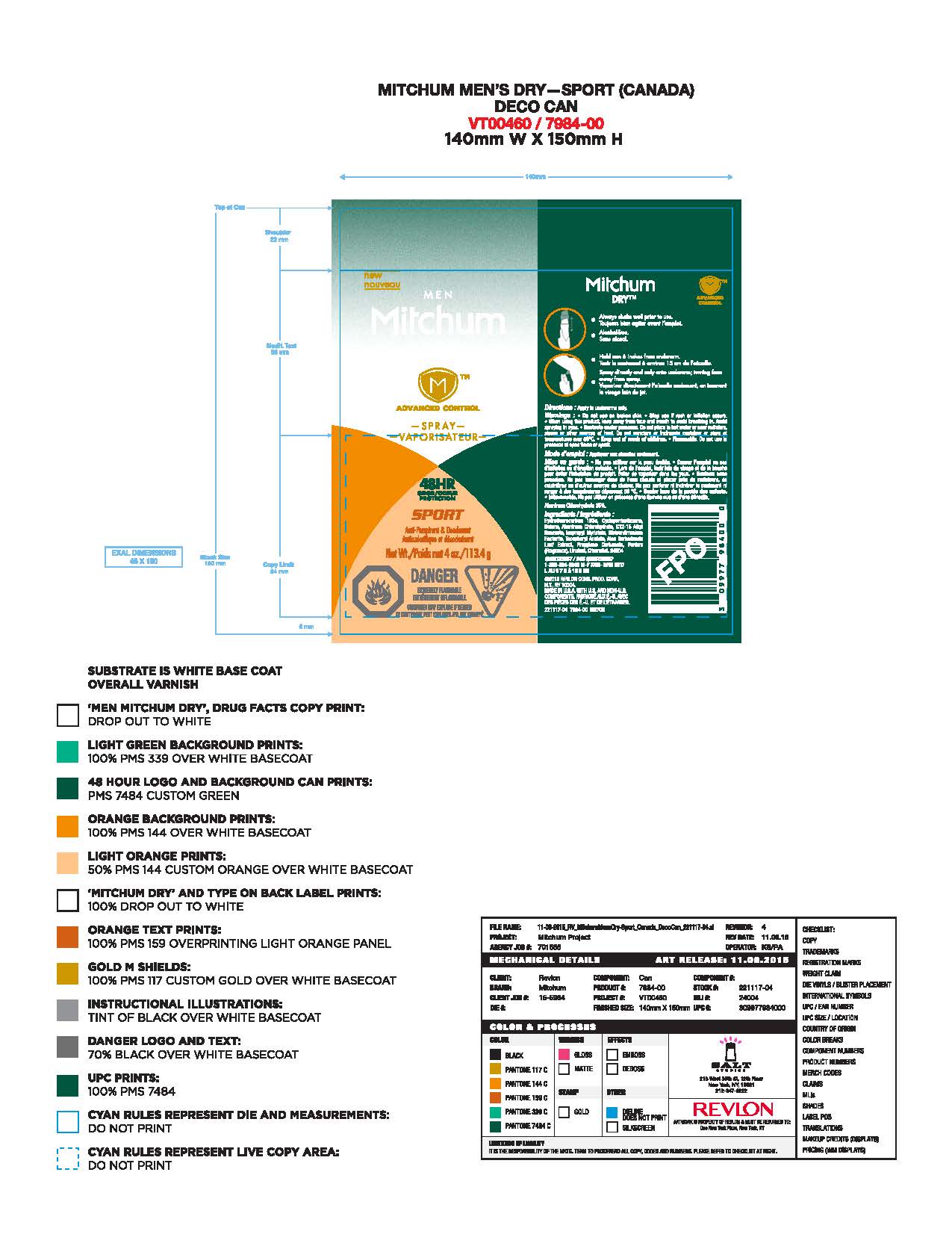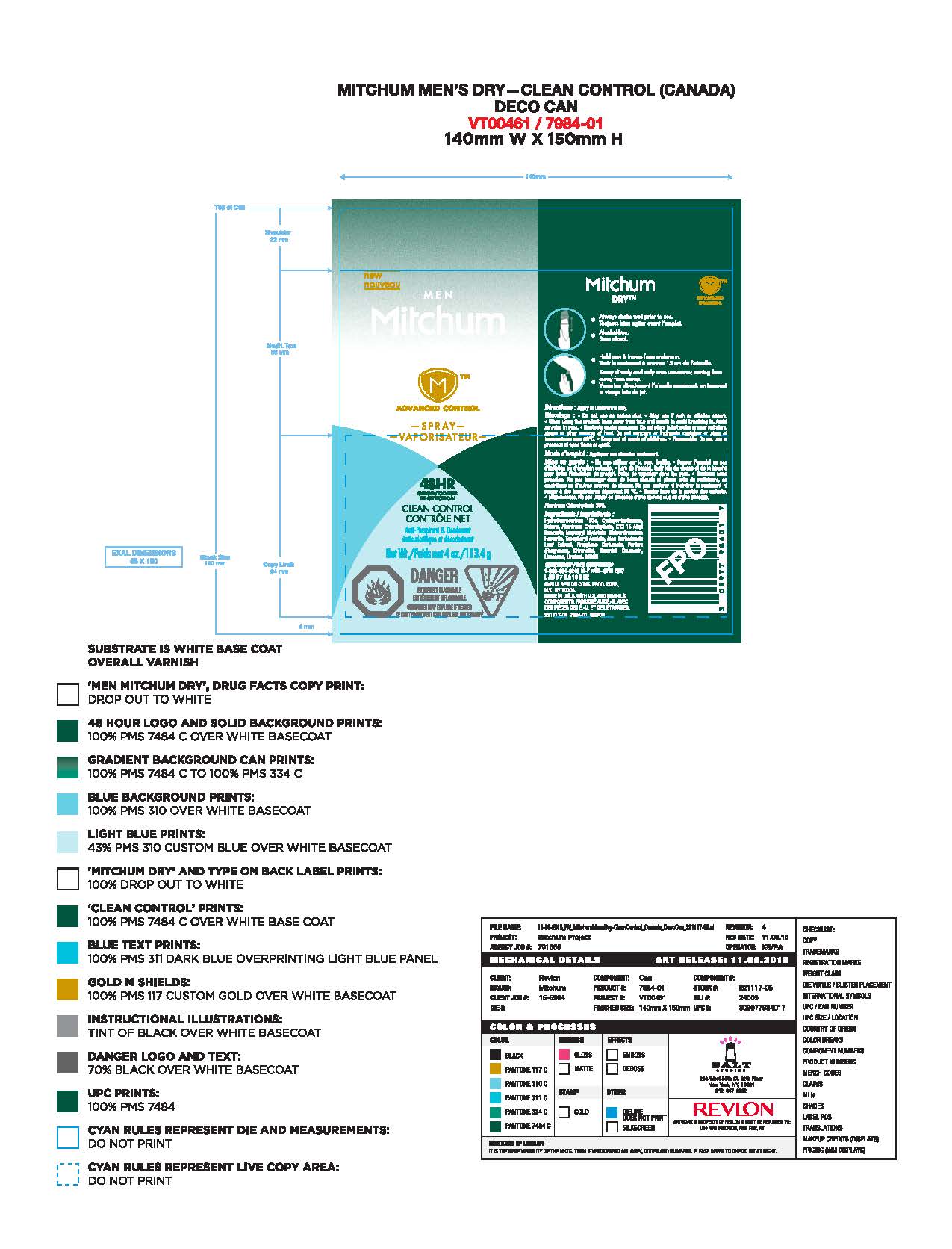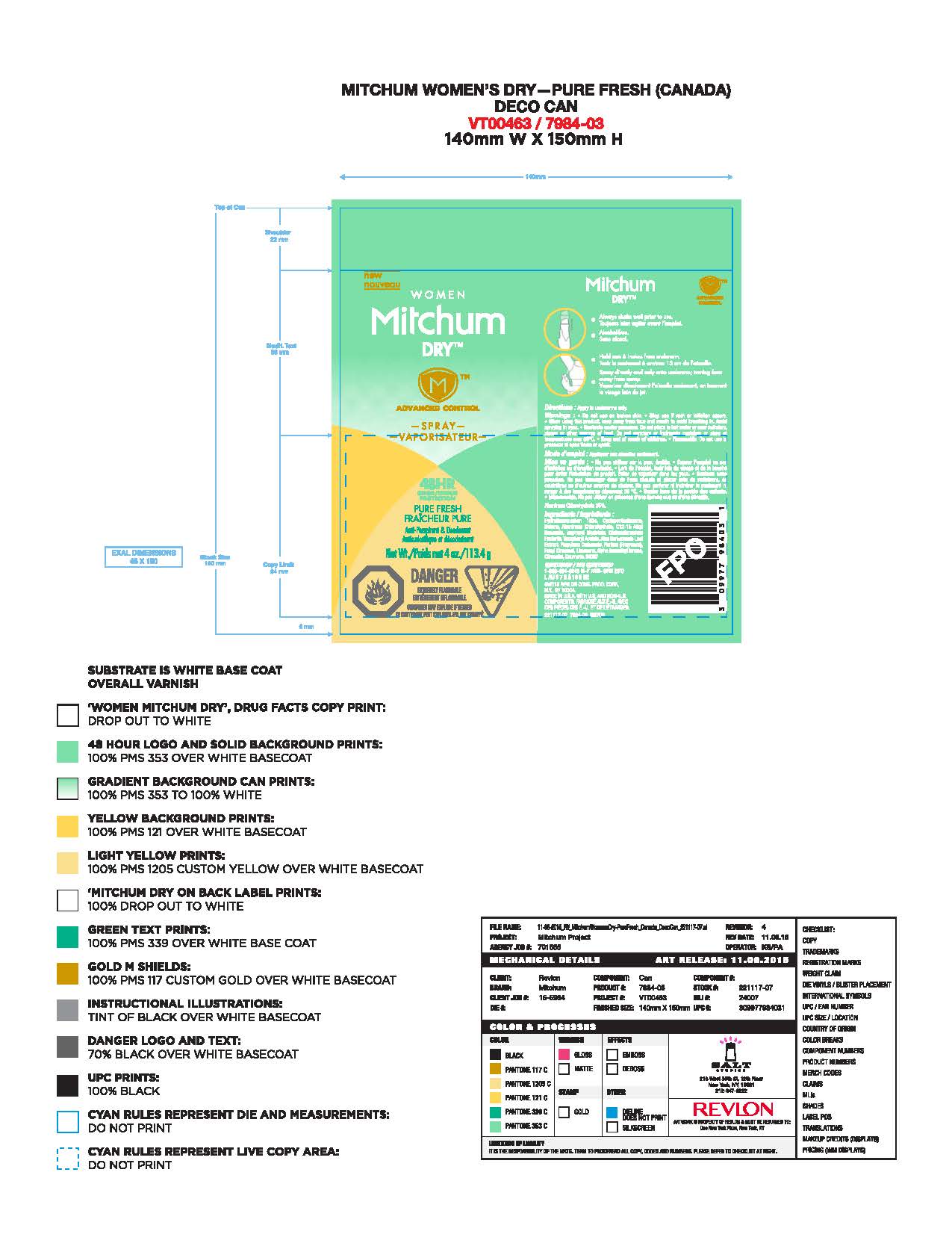 DRUG LABEL: Mitchum Advance Control
NDC: 10967-635 | Form: AEROSOL
Manufacturer: Revlon Consumer Products Corp
Category: otc | Type: HUMAN OTC DRUG LABEL
Date: 20161207

ACTIVE INGREDIENTS: ALUMINUM CHLOROHYDRATE 0.25 g/1 mL
INACTIVE INGREDIENTS: CYCLOMETHICONE 5; ALKYL (C12-15) BENZOATE; ISOPROPYL MYRISTATE; ALOE VERA LEAF; PROPYLENE CARBONATE; .BETA.-CITRONELLOL, (R)-; GERANIOL; COUMARIN; LIMONENE, (+)-; 1,1-DIFLUOROETHANE; BUTANE; DISTEARDIMONIUM HECTORITE; ALPHA-TOCOPHEROL ACETATE; LINALOOL, (+/-)-

Revlon Mitchum Aerosol

Active Ingredient

Aluminum Chlorohydrate 25.0%

Directions:

Apply to Underarms only

Warnings:

Do not use on broken skin

Stop Use if rash or irritation occurs.

When using this product, keep away from face and mouth to avoid breathing in.

Avoid spraying in eyes

Contents under pressure

Do not place in hot water or near radiators, stoves, or other sources of heat.

Do not puncture or incinerate container or store at temperatures over 50C

Flammable Do not use in presence of flame or spark.

Keep out of reach of children

Questions?

1-888-864-8248 M-F 7AM-6PM EST

Uses

Reduces underarm wetness

Purpose

Anti-Perspirant

Inactive Ingredients

Hydrofluorocarbon 152a,
Cyclopentasiloxane, Butane, C12-15 Alkyl Benzoate,
Isopropyl Myristate, Disteardimonium Hectorite,
Propylene Carbonate, Tocopheryl Acetate, Aloe
Barbadensis Leaf Extract, Parfum (Fragrance), Linalool,
Benzyl Salicylate, Citronellol, Hydroxycitronellal, Hexyl
Cinnamal, Limonene, Benzyl Benzoate, Geraniol,
Cinnamyl Alcohol, Alpha-Isomethyl Ionone. 24309